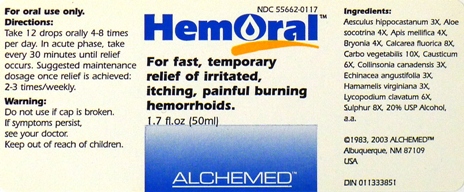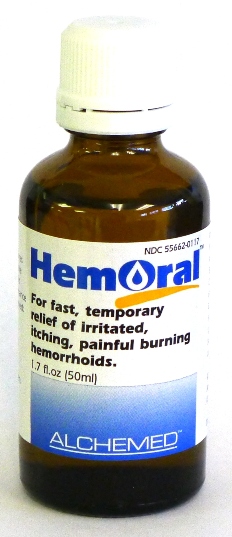 DRUG LABEL: HemOral
NDC: 55662-0117 | Form: LIQUID
Manufacturer: Alchemed
Category: homeopathic | Type: HUMAN OTC DRUG LABEL
Date: 20120101

ACTIVE INGREDIENTS: HORSE CHESTNUT 3 [hp_X]/1 mL; ALOE 4 [hp_X]/1 mL; APIS MELLIFERA 4 [hp_X]/1 mL; BRYONIA ALBA ROOT 4 [hp_X]/1 mL; CALCIUM FLUORIDE 8 [hp_X]/1 mL; ACTIVATED CHARCOAL 10 [hp_X]/1 mL; CAUSTICUM 6 [hp_X]/1 mL; COLLINSONIA CANADENSIS ROOT 3 [hp_X]/1 mL; ECHINACEA ANGUSTIFOLIA 3 [hp_X]/1 mL; HAMAMELIS VIRGINIANA ROOT BARK/STEM BARK 3 [hp_X]/1 mL; LYCOPODIUM CLAVATUM SPORE 6 [hp_X]/1 mL; SULFUR 8 [hp_X]/1 mL
INACTIVE INGREDIENTS: ALCOHOL

HemOral

Purpose:

For fast, temporary relief of irritated, itching, painful burning hemorrhoids.

Usage and Dosage:

For oral use only.

DOSAGE AND ADMINISTRATION

In Acute Phase:
12 drops, every 30 minutes until relief occurs
When Relief Occurs:
12 drops, 4-8 times per day
Maintenance dosage:
2-3 times weekly

Warnings:

Keep out of reach of children.

WARNINGS

If symptoms persist, see your doctor.
Do not use if cap is broken.

Active Ingredients:

Aesculus hippocastanum 3X, Aloe socotrina 4X, Apis mellifica 4X, Bryonia 4X, Calcarea fluorica 8X, Carbo vegetabilis 10X, Causticum 6X, Collinsonia canadensis 3X, Echinacea angustifolia 3X, Hamamelis virginiana 3X, Lycopodium clavatum 6X, Sulphur 8X

Inactive Ingredients:

Alcohol, 20% USP

QUESTIONS

1983, 2003 ALCHEMED, Albuquerque, NM 87109 USA

PACKAGE LABEL

HemOral Product

HemOral Bottle Label